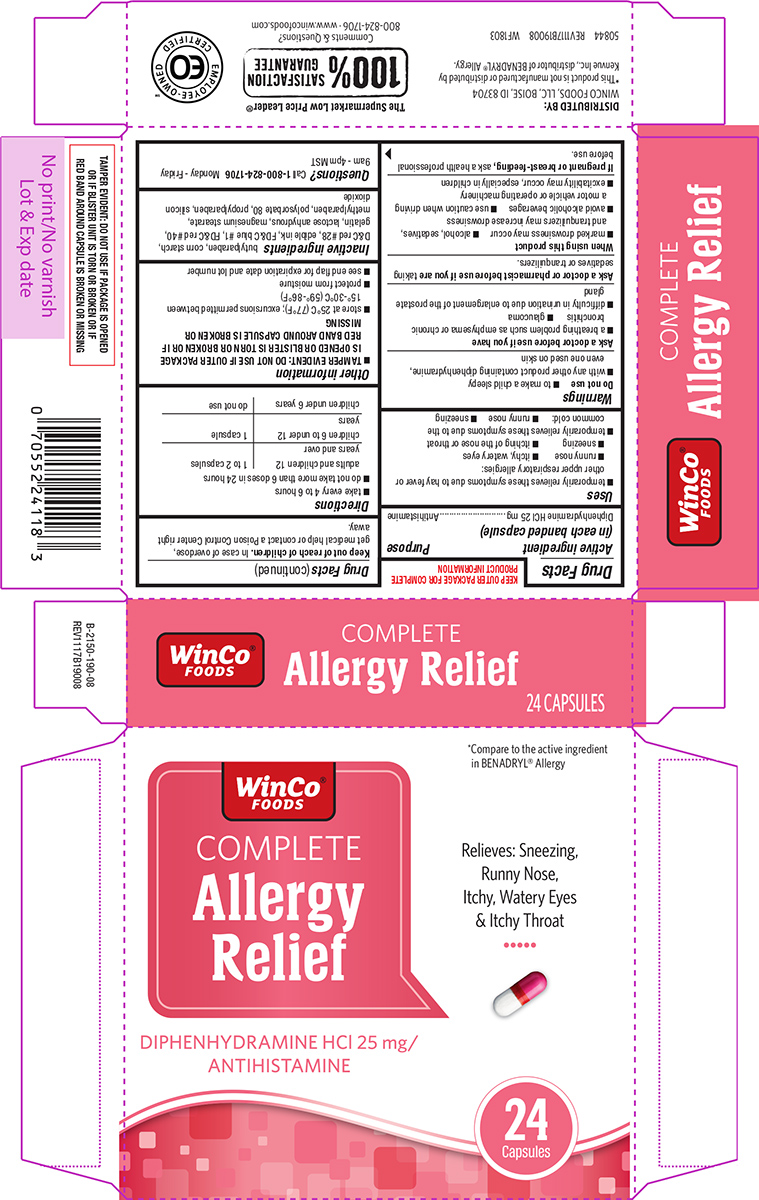 DRUG LABEL: Allergy Relief
NDC: 67091-201 | Form: CAPSULE
Manufacturer: WinCo Foods, LLC
Category: otc | Type: HUMAN OTC DRUG LABEL
Date: 20250718

ACTIVE INGREDIENTS: DIPHENHYDRAMINE HYDROCHLORIDE 25 mg/1 1
INACTIVE INGREDIENTS: BUTYLPARABEN; STARCH, CORN; D&C RED NO. 28; FD&C BLUE NO. 1; FD&C RED NO. 40; GELATIN, UNSPECIFIED; ANHYDROUS LACTOSE; MAGNESIUM STEARATE; METHYLPARABEN; POLYSORBATE 80; PROPYLPARABEN; SILICON DIOXIDE

Winco 44-190

Active ingredient (in each banded capsule)

Diphenhydramine HCl 25 mg

Purpose

Antihistamine

Uses

- temporarily relieves these symptoms due to hay fever or other upper respiratory allergies:
  - runny nose
  - itchy, watery eyes
  - sneezing
  - itching of the nose or throat
- temporarily relieves these symptoms due to the common cold:
  - runny nose
  - sneezing

Warnings

Do not use

- to make a child sleepy
- with any other product containing diphenhydramine, even one used on skin

Ask a doctor before use if you have

- a breathing problem such as emphysema or chronic bronchitis
- glaucoma
- difficulty in urination due to enlargement of the prostate gland

Ask a doctor or pharmacist before use if you are

taking sedatives or tranquilizers.

When using this product

- marked drowsiness may occur
- alcohol, sedatives, and tranquilizers may increase drowsiness
- avoid alcoholic beverages
- use caution when driving a motor vehicle or operating machinery
- excitability may occur, especially in children

If pregnant or breast-feeding,

ask a health professional before use.

Keep out of reach of children.

In case of overdose, get medical help or contact a Poison Control Center right away.

Directions

- take every 4 to 6 hours
- do not take more than 6 doses in 24 hours

adults and children 12 years and over | 1 to 2 capsules
children 6 to under 12 years | 1 capsule
children under 6 years | do not use

Other information

- TAMPER EVIDENT: DO NOT USE IF OUTER PACKAGE IS OPENED OR BLISTER IS TORN OR BROKEN OR IF RED BAND AROUND CAPSULE IS BROKEN OR MISSING
- store at 25ºC (77ºF); excursions permitted between 15º-30ºC (59º-86ºF)
- protect from moisture
- see end flap for expiration date and lot number

Inactive ingredients

butylparaben, corn starch, D&C red #28, edible ink, FD&C blue #1, FD&C red #40, gelatin, lactose anhydrous, magnesium stearate, methylparaben, polysorbate 80, propylparaben, silicon dioxide

Questions?

Call 1-800-824-1706 Monday - Friday 9am - 4pm MST

Principal Display Panel

WinCo®
FOODS

COMPLETE
Allergy
Relief

DIPHENHYDRAMINE HCl 25 mg/
ANTIHISTAMINE

*Compare to the active ingredient
in BENADRYL® Allergy

Relieves: Sneezing,
Runny Nose,
Itchy, Watery Eyes
& Itchy Throat

24
Capsules

TAMPER EVIDENT: DO NOT USE IF PACKAGE IS OPENED
OR IF BLISTER UNIT IS TORN OR BROKEN OR IF
RED BAND AROUND CAPSULE IS BROKEN OR MISSING

DISTRIBUTED BY:
WINCO FOODS, LLC, BOISE, ID 83704

*This product is not manufactured or distributed by
Kenvue Inc., distributor of BENADRYL® Allergy.

50844 REV1117B19008 WF1803

The Supermarket Low Price Leader®
100%
SATISFACTION
GUARANTEE
Comments & Questions?
800-824-1706 • www.wincofoods.com

EMPLOYEE-OWNED
EO
CERTIFIEDSM

Winco 44-190